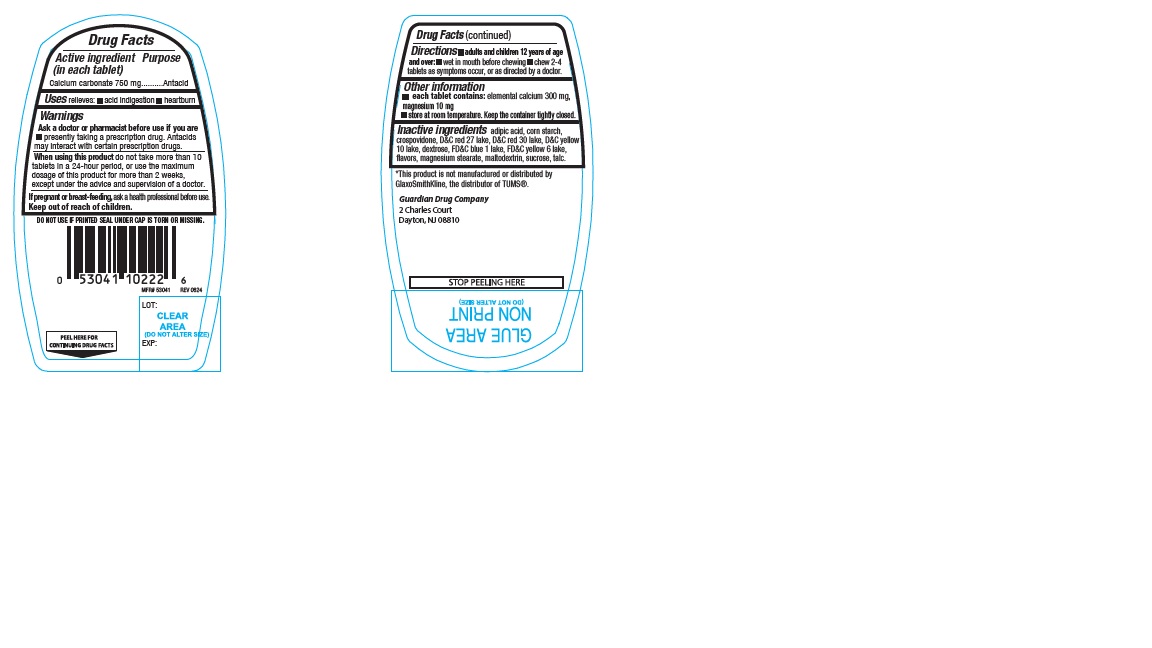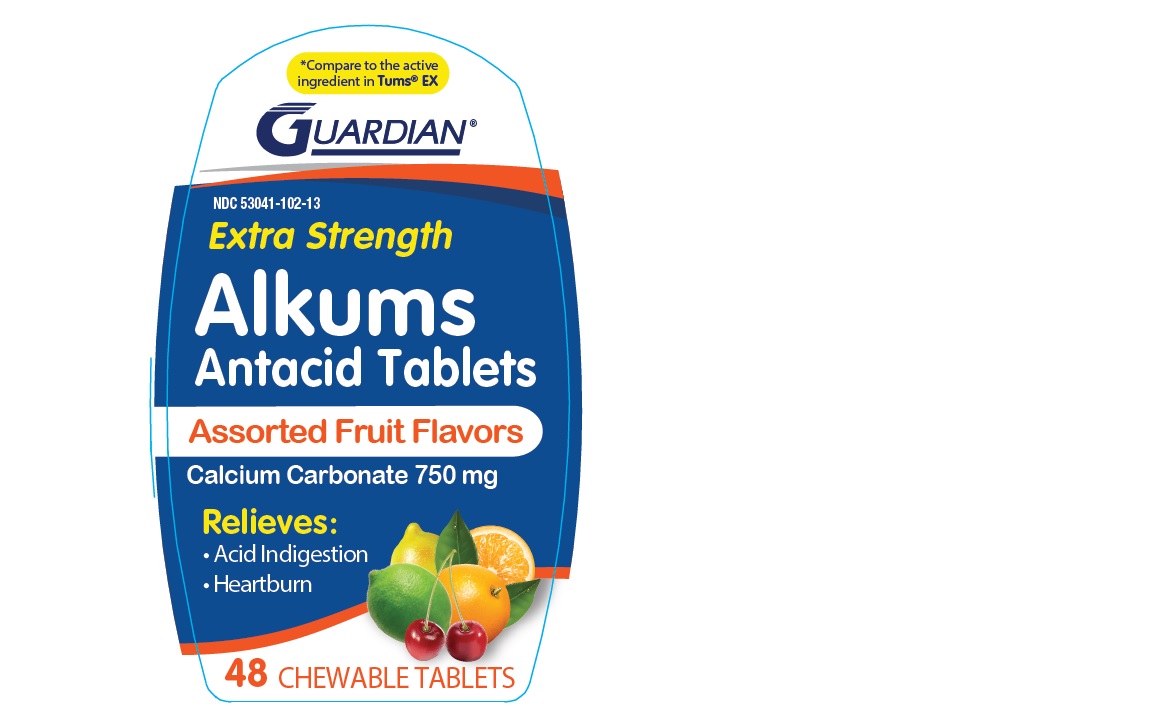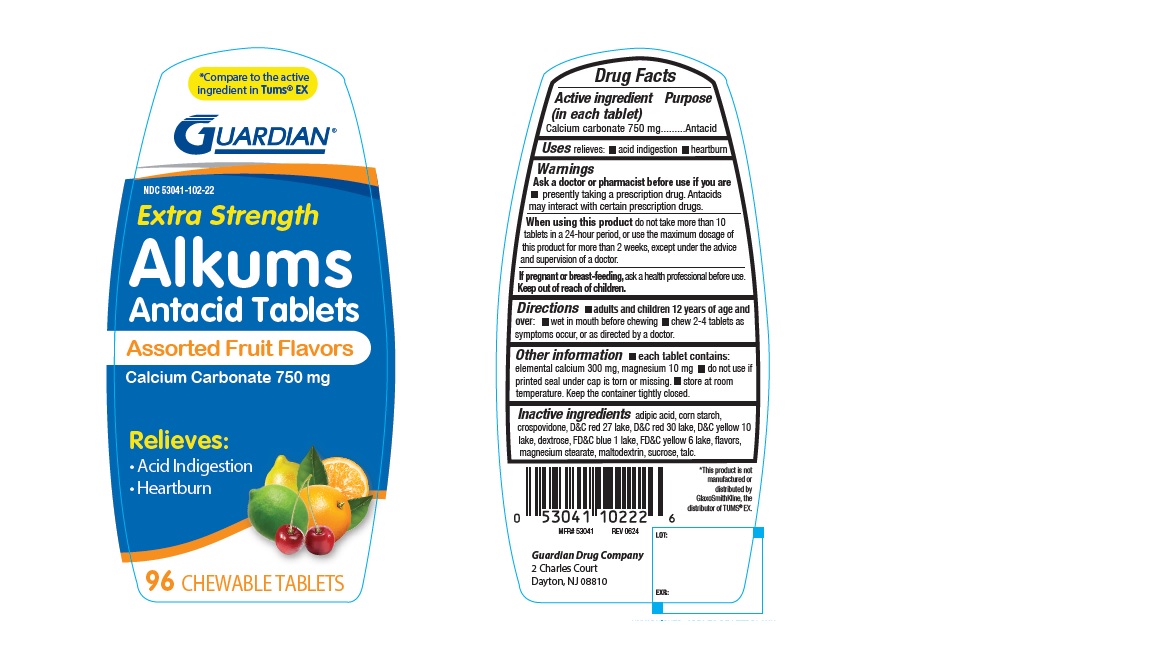 DRUG LABEL: GDC Extra strength Alkums Antacid 127AF
NDC: 53041-102 | Form: TABLET, CHEWABLE
Manufacturer: Guardian Drug Company
Category: otc | Type: Human OTC Drug Label
Date: 20240813

ACTIVE INGREDIENTS: CALCIUM CARBONATE 750 mg/1 1
INACTIVE INGREDIENTS: ADIPIC ACID; STARCH, CORN; CROSPOVIDONE; D&C RED NO. 27 ALUMINUM LAKE; D&C RED NO. 30 ALUMINUM LAKE; D&C YELLOW NO. 10 ALUMINUM LAKE; DEXTROSE; FD&C BLUE NO. 1 ALUMINUM LAKE; FD&C YELLOW NO. 6 ALUMINUM LAKE; MAGNESIUM STEARATE; SUCROSE; TALC; MALTODEXTRIN

GDC Extra Strength Alkums Antacid 127AF

ACTIVE INGREDIENT(S)

Calcium carbonate 750 mg

PURPOSE

Antacid

USE(S)

relieves:

acid indigestion

heartburn

WARNINGS

.

ASK A DOCTOR OR PHARMACIST BEFORE USE IF YOU ARE

presently taking a prescription drug. Antacids may interact with certain prescription drugs.

WHEN USING THIS PRODUCT

do not take more than 10 tablets in a 24 hour period, or use the maximum dosage of this product for more than 2 weeks, under the advice and supervision of a doctor.

IF PREGNANCY/BREAST-FEEDING,

ask a health professional before use.

KEEP OUT OF REACH OF CHILDREN

.

DIRECTIONS

- adults and children 12 years age and over:
- wet in mouth before chewing
- chew 2-4 tablets as symptoms occur, or as directed by a doctor.

OTHER INFORMATION

- each tablet contains: elemental calcium 300 mg , magnesium 10 mg
- store at room temperature. Keep the container tightly closed.

INACTIVE INGRADIENTS

adipic acid, corn starch, crospovidone, d&c red 27 lake, D&C red 30 lake, D&C yellow 10 lake, dextrose , FD&C blue 1 lake, FD&C yellow 6 lake, flavors, magnesium stearate, maltodextrin, sucrose, talc

PRINCIPAL DISPLAY PANEL

*Compare to the active ingredient in TUMS® EX

GUARDIAN®

NDC 53041-102-22

Extra Strength

Alkums Antacid Tablets

Assorted Fruit Flavors

Calcium Carbonate 750 mg

Relieves :

- Acid Indigestion
- Heartburn

96 CHEWABLE TABLETS

*Compare to the active ingredient in TUMS® EX

GUARDIAN®

NDC 53041-102-13

Extra Strength Alkums Antacid Tablets

Assorted Fruit Flavors

Calcium Carbonate 750 mg

Relieves :

- Acid Indigestion
- Heartburn

48 CHEWABLE TABLETS